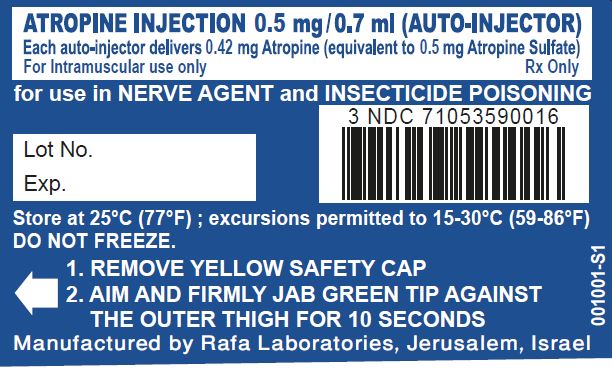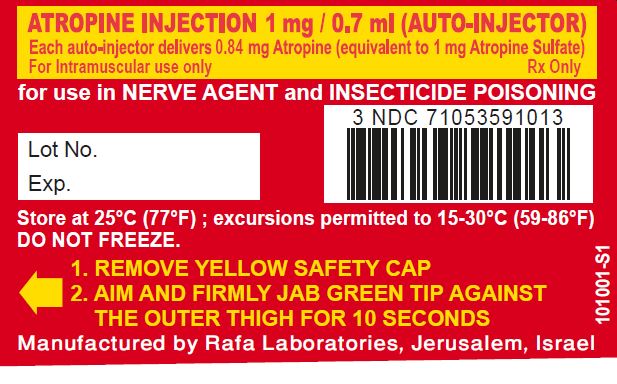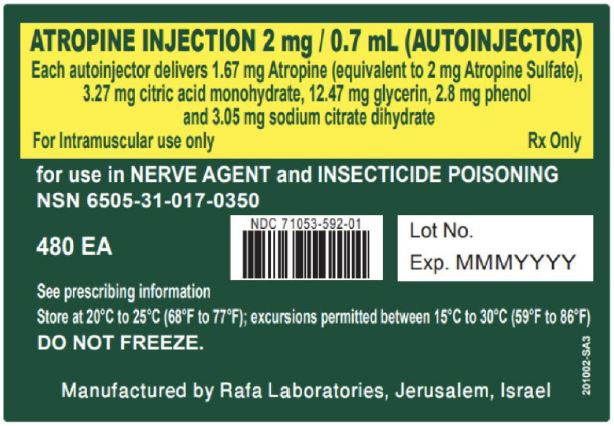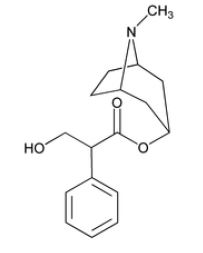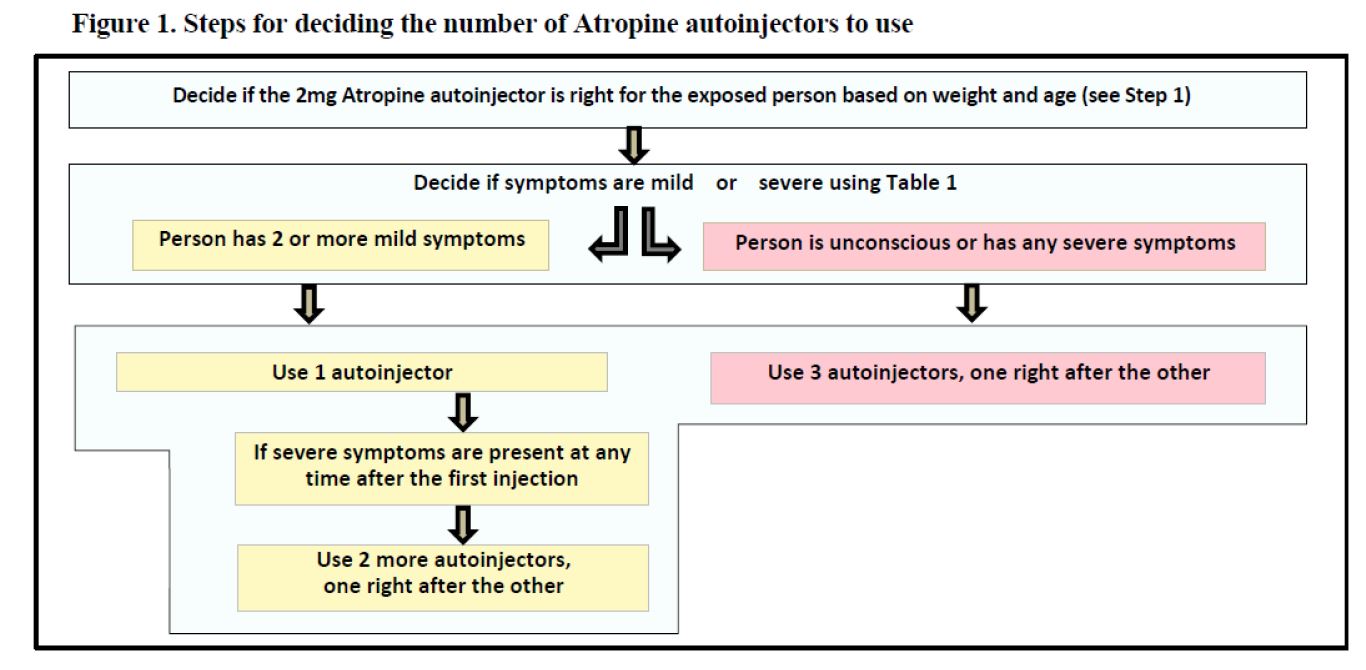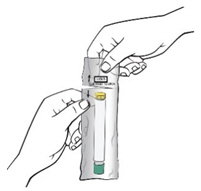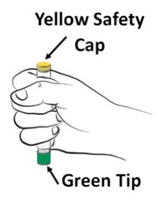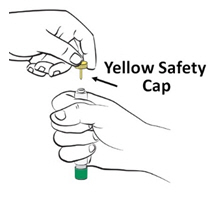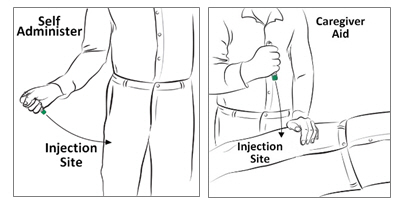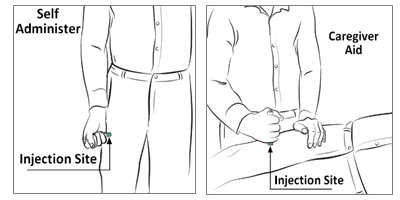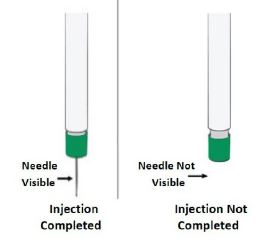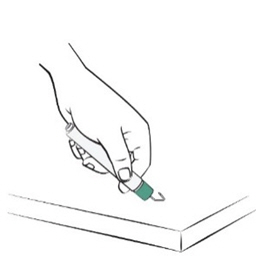 DRUG LABEL: N/A
NDC: 71053-591 | Form: INJECTION
Manufacturer: Rafa Laboratories, Ltd.
Category: prescription | Type: HUMAN PRESCRIPTION DRUG LABEL
Date: 20260218

ACTIVE INGREDIENTS: ATROPINE 1 mg/0.7 mL

HIGHLIGHTS OF PRESCRIBING INFORMATION

These highlights do not include all the information needed to use ATROPINE safely and effectively. See full prescribing information for ATROPINE.
ATROPINE injection, for intramuscular use
Initial U.S. Approval: 1973

INDICATIONS AND USAGE

Atropine, a cholinergic muscarinic antagonist, is indicated for the treatment of poisoning by susceptible organophosphorus nerve agents having anticholinesterase activity as well as organophosphorus or carbamate insecticides in adults and pediatric patients weighing more than 41 kg (90 pounds) (1).

- Atropine is intended as an initial treatment as soon as symptoms appear; definitive medical care should be sought immediately. (2.1)
- Administer each dose of the 2 mg Atropine autoinjector into the patient’s mid-lateral outer thigh (2.1).
- Dosage for Mild Symptoms: If the patient experiences two or more mild symptoms, administer one injection intramuscularly into the mid-lateral thigh. If, at any time after the first dose, the patient develops any of the severe symptoms, administer two additional injections intramuscularly in rapid succession (2.2).
- Dosage for Severe Symptoms: If a patient has any of the severe symptoms, immediately administer three injections intramuscularly into the patient's mid-lateral thigh in rapid succession (2.2).

DOSAGE FORMS AND STRENGTHS

Injection: 1.67 mg/0.7 mL atropine base (equivalent to 2 mgatropine sulfate) in a single-dose prefilled autoinjector (3)

CONTRAINDICATIONS

None (4)

WARNINGS AND PRECAUTIONS

- Cardiovascular (CV) Risks: Tachycardia, palpitations, premature ventricular contractions, flutter, fibrillation, etc. Use caution in patients with known CV disease or conduction problems. (5.1)
- Heat Injury:May inhibit sweating and lead to hyperthermia; avoid excessive exercising and heat exposure. (5.2)
- Acute Glaucoma: May precipitate in susceptible individuals. (5.3)
- Urinary Retention: Administer with caution in patient with bladder outflow obstruction. (5.4)
- Pyloric Stenosis: May convert into complete obstruction. (5.5)
- Exacerbation of Chronic Lung Disease: Atropine may cause inspiration of bronchial secretions and formation of dangerous viscid plugs in individuals with chronic lung disease; monitor respiratory status. (5.6)
- Hypersensitivity: Atropine may cause hypersensitivity reactions, including anaphylaxis (5.7)

ADVERSE REACTIONS

Mild to moderate pain may be experienced at the site of injection. Common adverse reactions of atropine include dryness of the mouth, blurred vision, dry eyes, photophobia, confusion, headache, dizziness, tachycardia, palpitations, flushing, urinary hesitance or retention, constipation, abdominal pain, abdominal distention, nausea, vomiting, loss of libido, and impotency (6.1, 6.2).

To report SUSPECTED ADVERSE REACTIONS, contact Rafa Laboratories at 1-386-418-7911 or FDA at 1-800-FDA-1088 or www.fda.gov/medwatch

DRUG INTERACTIONS

Pralidoxime: may potentiate the effect of atropine (7.1).

Barbiturates: atropine may potentiate the effect of barbiturates (7.2)

See 17 for PATIENT COUNSELING INFORMATION and FDA-approved patient labeling.

FULL PRESCRIBING INFORMATION

INDICATIONS AND USAGE

Atropine is indicated for the treatment of poisoning by susceptible organophosphorus nerve agents having anticholinesterase activity as well as organophosphorus or carbamate insecticides in adults and pediatric patients weighing more than 41 kg (90 pounds).

Important Administration Information

- Three (3) Atropine autoinjectors should be available for use in each patient at risk for nerve agent or organophosphate insecticide poisoning; one (1) for mild symptoms plus two (2) more for severe symptoms [see Dosage and Administration (2.2)].
- Only administer Atropine to patients experiencing symptoms of organophosphorus poisoning in a situation where exposure is known or suspected. The Atropine autoinjector is intended as an initial treatment of the muscarinic symptoms of insecticide or nerve agent poisonings as soon as symptoms appear; definitive medical care should be sought immediately.
- In general, atropine should not be used until cyanosis has been overcome since atropine may produce ventricular fibrillation and possible seizures in the presence of hypoxia.
- The Atropine autoinjector should be used by persons who have had adequate training in the recognition and treatment of nerve agent or insecticide intoxication, but may be administered by a caregiver or by self-administration if a trained provider is not available.
- Close supervision of all treated patients is indicated for at least 48 to 72 hours.
- In severe poisonings, concurrent administration of an anticonvulsant (preferably a benzodiazepine) may be warranted if seizure is suspected in the unconscious individual because overt jerking may not be apparent because of the effects of the poison [see Drug Interactions (7.2)].
- In poisonings caused by organophosphorous nerve agents and insecticides it may also be helpful to concurrently administer a cholinesterase reactivator such as pralidoxime chloride [see Drug Interactions (7.1)].
- The injection site is the mid-lateral thigh area. The Atropine autoinjector can inject through clothing. However, make sure pockets at the injection site are empty. People who may not have a lot of fat at the injection site should also be injected in the mid-lateral thigh, but before giving the injection, bunch up the thigh to provide a thicker area for injection.

Dosage Information

Dosage for Mild Symptoms in Adults and Pediatric Patients Weighing More Than 41 kg (90 Pounds)

First Dose: If the patient experiences two or more mild symptoms of nerve agent (nerve gas) or insecticide exposure listed in Table 1, administer one(1) Atropine injection intramuscularly into the mid-lateral outer thigh.

Additional Doses: If, at any time after the first dose, the patient develops any of the severe symptoms listed in Table 1, administer two (2) additional Atropine injections intramuscularly in rapid succession.

Wait 10 to 15 minutes for Atropine to take effect. If, after 10 to 15 minutes, the patient does not develop any of the severe symptoms listed in Table 1, no additional Atropine injections are recommended.

If possible, a person other than the patient should administer the second and third 2 mg Atropine autoinjectors.

Dosage for Severe Symptoms in Adults and Pediatric Patients Weighing More Than 41 kg (90 Pounds)

If a patient is either unconscious or has any of the severe symptoms listed in Table 1, immediately administer three (3) Atropine injections intramuscularly into the patient’s mid-lateral outer thigh in rapid succession.

Table 1: Common Signs/Symptoms of Organophosphorus and/or Carbamate Poisoning
MILD symptoms include:; - Blurred vision or miosis - Unexplained excessive lacrimation - Unexplained excessive nasopharyngeal secretions - Increased salivation - Chest tightness, difficulty breathing, wheezing, or coughing - Tremors throughout the body or muscular twitching - Nausea, vomiting, abdominal cramping, or diarrhea - Tachycardia or bradycardia | SEVERE symptoms include:; - Altered mental status - Loss of consciousness - Respiratory distress - Excessive secretions from the lungs/airway - Severe muscular twitching, generalized weakness or paralysis - Involuntary urination and/or defecation - Convulsions or seizures

Additional Care Instructions

Environmental

All patients should be evacuated immediately from the contaminated environment.
Protective masks and clothing should be used when available.
Aggressive and safe decontamination procedures should be undertaken as soon as possible.
If dermal exposure has occurred, clothing should be removed and the hair and skin washed thoroughly with sodium bicarbonate or alcohol as soon as possible.
Physicians and/or other medical personnel assisting evacuated patients of nerve and insecticide poisoning should avoid exposing themselves to contamination by the patient’s clothing.

Medical

Medical help should be sought immediately.
Emergency care of the severely poisoned individual should include removal of oral and bronchial secretions, maintenance of a patent airway, supplemental oxygen and, if necessary, artificial ventilation.
Severe difficulty in breathing requires artificial respiration in addition to the use of Atropine since Atropine is not dependable in reversing the weakness or paralysis of the respiratory muscles.

Refer to the illustrated dose-specific Instructions for Use for autoinjector administration instructions.
Antidotes, such as Atropine, should not be relied upon solely to provide complete protection from chemical nerve agents and insecticide poisoning.

DOSAGE FORMS AND STRENGTHS

Each single-dose Atropine autoinjector contains atropine base 1.67 mg/0.7 mL (equivalent to atropine sulfate 2 mg/0.7 mL) in a sterile solution for intramuscular injection.

CONTRAINDICATIONS

None.

WARNINGS AND PRECAUTIONS

Cardiovascular Risks

Cardiovascular adverse reactions reported in the literature for atropine include, but are not limited to, sinus tachycardia, palpitations, premature ventricular contractions, atrial flutter, atrial fibrillation, ventricular flutter, ventricular fibrillation, cardiac syncope, asystole, and myocardial infarction [see Adverse Reactions (6)]. In patients with a recent myocardial infarction and/or severe coronary artery disease, there is a possibility that atropine-induced tachycardia may cause ischemia, extend or initiate myocardial infarcts, and stimulate ventricular ectopy and fibrillation. Atropine should be used with caution in patients with known cardiovascular disease or cardiac conduction problems.

Heat Injury

Atropine may inhibit sweating which, in a warm environment or with excessive exercise, can lead to hyperthermia and heat injury. To the extent feasible, avoid excessive exercise and heat exposure [see Adverse Reactions (6)].

Acute Glaucoma

Atropine may cause acute glaucoma and should be administered with caution in patients at risk for acute glaucoma or who have severe narrow angle glaucoma. Monitor for signs and symptoms of intraocular pressure, as appropriate.

Urinary Retention

Atropine may cause urinary retention and should be administered with caution to patients with clinically significant bladder outflow obstruction.

Pyloric Stenosis

Atropine may cause complete pyloric obstruction in patients with partial pyloric stenosis. These patients should be monitored for gastrointestinal symptoms following administration of Atropine.

Exacerbation of Chronic Lung Disease

Atropine may cause thickening of bronchial secretions and formation of dangerous viscid plugs in individuals with chronic lung disease. Respiratory status should be monitored in individuals with chronic lung disease following administration of Atropine.

Hypersensitivity

Atropine can cause hypersensitivity reactions, including anaphylactic reactions [see Adverse Reactions (6)]. Medical supervision is necessary in patients who have had previous anaphylactic reactions to atropine and require treatment for organophosphorus or nerve agent poisoning.

ADVERSE REACTIONS

The following serious adverse reactions are described elsewhere in the labeling:

- Cardiovascular Risks [ see Warnings and Precautions (5.1)]
- Heat Injury [ see Warnings and Precautions (5.2)]
- Acute Glaucoma [ see Warnings and Precautions (5.3)]
- Urinary Retention [ see Warnings and Precautions (5.4)]
- Pyloric Stenosis [ see Warnings and Precautions (5.5)]
- Exacerbation of Chronic Lung Disease [ see Warnings and Precautions (5.6)]
- Hypersensitivity [ see Warnings and Precautions (5.7)]

The following adverse reactions associated with the use of atropine were identified in the literature. Because these reactions are reported voluntarily from a population of uncertain size, it is not always possible to reliably estimate their frequency or establish a causal relationship to drug exposure.
Injection Site Reactions

Mild to moderate pain may be experienced at the site of injection.

Adverse Reactions at Recommended Dosages

The major and most common side effects of atropine can be attributed to its antimuscarinic action. These include dryness of the mouth, blurred vision, dry eyes, photophobia, confusion, headache, dizziness, fatigue, tachycardia, palpitations, flushing, urinary hesitance or retention, constipation, abdominal pain, abdominal distention, nausea, vomiting, loss of libido, and impotency. Anhidrosis may produce heat intolerance and impairment of temperature regulation especially in a hot environment.

Hypersensitivity

Hypersensitivity reactions will occasionally occur with atropine; these are usually seen as skin rashes, on occasion progressing to exfoliation. Anaphylactic reactions have occurred.

Additional Adverse Reactions to Atropine by Organ System

The following adverse reactions were reported in published literature for atropine in both adults and pediatric patients:

Cardiovascular: Sinus tachycardia, supraventricular tachycardia, junctional tachycardia, ventricular tachycardia, bradycardia, palpitations, ventricular arrhythmia, ventricular flutter, ventricular fibrillation, atrial arrhythmia, atrial fibrillation, atrial ectopic beats, ventricular premature contractions, bigeminal beats, trigeminal beats, nodal extrasystole, ventricular extrasystole, supraventricular extrasystole, asystole, cardiac syncope, prolongation of sinus node recovery time, cardiac dilation, left ventricular failure, myocardial infarction, intermittent nodal rhythm (no P wave), prolonged P wave, shortened PR segment, R on T phenomenon, shortened RT duration, widening and flattening of QRS complex, prolonged QT interval, flattening of T wave, repolarization abnormalities, altered ST-T waves, retrograde conduction, transient AV dissociation, increased blood pressure, decreased blood pressure, labile blood pressure, weak or impalpable peripheral pulses.

Eye: Mydriasis, pupils poorly reactive to light, decreased contrast sensitivity, decreased visual acuity, decreased accommodation, cycloplegia, strabismus, heterophoria, cyclophoria, acute angle closure glaucoma, conjunctivitis, keratoconjunctivitis sicca, blindness, tearing, dry conjunctiva, irritated eyes, crusting of eyelid, blepharitis.

Gastrointestinal: Paralytic ileus, decreased bowel sounds, delayed gastric emptying, decreased food absorption, dysphagia.

General: Hyperpyrexia, lethargy, somnolence, chest pain, excessive thirst, weakness, syncope, insomnia, tongue chewing, dehydration, feeling hot.

Special Investigations: Leukocytosis, hyponatremia, elevated BUN, elevated hemoglobin, elevated erythrocytes, low hemoglobin, hypoglycemia, hyperglycemia, hypokalemia, increase in photic stimulation on EEG, signs of drowsiness on EEG, runs of alpha waves on EEG, alpha waves (EEG) blocked upon opening eyes.

Metabolic: Failure to feed.

Central Nervous System: Ataxia, hallucinations (visual or aural), seizures (generally tonic-clonic), abnormal movements, coma, stupor, amnesia, diminished tendon reflexes, hyperreflexia, muscle twitching, opisthotnos, Babinski's reflex/Chaddock's reflex, hypertonia, dysmetria, muscle clonus, sensation of intoxication, difficulty concentrating, vertigo, dysarthria.

Psychiatric: Agitation, restlessness, delirium, paranoia, anxiety, mental disorders, mania, withdrawn behavior, behavior changes.

Genitourinary: Difficulty in micturation, urine urgency, distended urinary bladder, bed-wetting.

Pulmonary: Tachypnea, slow respirations, shallow respirations, breathing difficulty, labored respirations, inspiratory stridor, laryngitis, laryngospasm, pulmonary edema, respiratory failure, subcostal recession.

Dermatologic: Dry mucous membranes, dry warm skin, oral lesions, dermatitis, petechiae, rash, macular rash, papular rash, maculopapular rash, scarlatiniform rash, erythematous rash, sweating/moist skin, cold skin, cyanosed skin, salivation.

Adverse Reactions Caused by Inadvertent Injection

Administering additional 2 mg Atropine autoinjectors by mistake in the absence of actual nerve agent or insecticide poisoning may cause an overdose of atropine which could result in temporary incapacitation (inability to walk properly, see clearly or think clearly for several or more hours). Patients with cardiac disease may be at risk for serious adverse events, including death.

Adverse Reactions Observed in Pediatric Patients after Inappropriate Administration of Atropine

Amitai et al. (JAMA 1990) evaluated the safety of an atropine autoinjector in a case series of 240 children who received the atropine inappropriately (i.e., no nerve agent exposure) during the 1990 Gulf War Period. Overall, severity of atropinization followed a nonlinear correlation with dose. Estimated doses up to 0.045 mg/kg produced no signs of atropinization. Estimated doses between 0.045 mg/kg to 0.175 mg/kg and even greater than 0.175 mg/kg were associated with mild and severe effects respectively. Actual dosage received by children may have been considerably lower than estimated since incomplete injection in many cases was suspected. Regardless, adverse events reported were generally mild and self-limited. Few children required hospitalization. Adverse reactions reported were dilated pupils (43%), tachycardia (39%), dry membranes (35%), flushed skin (20%), temperature 37.8° C or 100° F (4%), and neurologic abnormalities (5%). There was also local pain and swelling. In patients with electrocardiograms, 22 of 91 (24%) children had severe tachycardia of 160-190 bpm. Neurologic abnormalities consisted of irritability, agitation, confusion, lethargy, and ataxia. Atropine 2mg is only approved for pediatric patients weighing more than 41kg at the recommended dosing.

DRUG INTERACTIONS

Pralidoxime

When atropine and pralidoxime are used together, the signs of atropinization (flushing, mydriasis, tachycardia, dryness of the mouth and nose) may occur earlier than might be expected when atropine is used alone because pralidoxime may potentiate the effect of atropine. Excitement and manic behavior immediately following recovery of consciousness have been reported in several cases. However, similar behavior has occurred in cases of organophosphate poisoning that were not treated with pralidoxime.

Barbiturates

Barbiturates are potentiated by the anticholinesterases; therefore, barbiturates should be used cautiously in the treatment of convulsions resulting from exposure to Atropine.

USE IN SPECIFIC POPULATIONS

Pregnancy

Risk Summary

Atropine readily crosses the placental barrier and enters fetal circulation. There are no adequate data on the developmental risk associated with the use of atropine in pregnant women. Adequate animal reproduction studies have not been conducted with atropine.

In the U.S. general population, the estimated background risk of major birth defects and miscarriage in clinically recognized pregnancies is 2% to 4% and 15% to 20%, respectively. The background risk of major birth defects and miscarriage for the indicated population is unknown.

Lactation

Risk Summary

Atropine has been reported to be excreted in human milk. There are no data on the effects of atropine on the breastfed infant or the effects of the drug on milk production. The developmental and health benefits of breastfeeding should be considered along with the mother’s clinical need for Atropine and any potential adverse effects on the breastfed infant from Atropine or from the underlying maternal condition.

Pediatric Use

Safety and effectiveness of the 2 mg Atropine autoinjector in pediatric patients weighing less than or equal to 41 kg (90 pounds) have not been established.

Safety and effectiveness of atropine in patients weighing more than 41 kg (90 pounds) are supported by published literature. Adverse reactions seen in pediatric patients are similar to those that occur in adult patients. However, central nervous system effects are often seen earlier, and pediatric patients may be more susceptible to the pharmacologic effects of atropine [see Adverse Reactions (6)].

Although the 2 mg Atropine autoinjector is not approved for pediatric patients less than 41 kg, overheating (atropine fever) caused by suppression of sweat gland activity may be more pronounced in infants and small children. Extreme hyperthermia in a newborn has been reported with as little as 0.065 mg orally.

Geriatric Use

Geriatric patients may be more susceptible to the pharmacologic effects of atropine [see Adverse Reactions (6)].

OVERDOSAGE

Symptoms

Manifestations of atropine overdose are dose-related and include flushing, dry skin and mucous membranes, tachycardia, widely dilated pupils that are poorly responsive to light, blurred vision, and fever (which can sometimes be dangerously elevated). Locomotor difficulties, disorientation, hallucinations, delirium, confusion, agitation, coma, and central depression can occur and may last 48 hours or longer. In instances of severe atropine intoxication, respiratory depression, coma, circulatory collapse, and death may occur.

Treatment

Supportive treatment should be administered as indicated. If respiration is depressed, artificial respiration with oxygen is necessary. Ice bags, alcohol sponges, or a hypothermia blanket may be required to reduce fever, especially in pediatric patients. Catheterization may be necessary if urinary retention occurs. Since atropine elimination takes place through the kidney, urinary output must be maintained and increased if possible; however, dialysis has not been shown to be helpful in overdose situations. Intravenous fluids may be indicated. Because of atropine-induced photophobia, the room should be darkened.

A benzodiazepine may be needed to control marked excitement and convulsions. However, large doses for sedation should be avoided because the central nervous system depressant effect may coincide with the depressant effect occurring late in severe atropine poisoning. Barbiturates are potentiated by the anticholinesterases; therefore, barbiturates should be used cautiously in the treatment of convulsions. Central nervous system stimulants are not recommended.

DESCRIPTION

The Atropine prefilled autoinjector is a single dose, self-contained unit designed for self or caregiver administration.

Each 2 mg Atropine autoinjector delivers 1.67 mg atropine (equivalent to 2 mg atropine sulfate) in 0.7 mL of sterile pyrogen-free solution for intramuscular injection. Each 2 mg autoinjector also contains the following inactive ingredients: 3.27 mg citric acid monohydrate (buffer), 12.47 mg glycerin, 2.8 mg phenol, and 3.05 mg sodium citrate dihydrate (buffer). The pH range is 4.1 - 4.5.

Atropine, a cholinergic muscarinic antagonist, occurs as white crystals, usually needle-like, or as a white, crystalline powder. It is highly soluble in water with a molecular weight of 289.38. Atropine, a naturally occurring belladonna alkaloid, is a racemic mixture of equal parts of d- and l-hyoscyamine; its activity is due almost entirely to the levo isomer of the drug.

Chemically, atropine is designated as 1αH,5αH-tropan-3–ol (±)-tropate (ester). Its empirical formula is C17H23NO3 and its structural formula is:

CLINICAL PHARMACOLOGY

Mechanism of Action

Atropine competitively blocks the effects of acetylcholine, including excess acetylcholine due to organophosphorus poisoning, at muscarinic cholinergic receptors on smooth muscle, cardiac muscle, secretory gland cells, and in peripheral autonomic ganglia and the central nervous system.

Pharmacodynamics

Atropine reduces secretions in the mouth and respiratory passages, relieves the constriction and spasm of the respiratory passages, and may reduce the paralysis of respiration that results from toxic nerve agents which increase anticholinesterase activity in the central nervous system. Atropine- induced parasympathetic inhibition may be preceded by a transient phase of stimulation, especially on the heart where small doses first slow the rate before characteristic tachycardia develops because of paralysis of vagal control. Although mild vagal excitation occurs, the increased respiratory rate and occasionally increased depth of respiration produced by atropine are more probably the result of bronchiolar dilatation. Accordingly, atropine is an unreliable respiratory stimulant, and large or repeated doses may depress respiration.

Adequate doses of atropine can prevent or abolish various types of reflex vagal cardiac slowing or asystole. The drug also can prevent or abolish bradycardia or asystole produced by injection of choline esters, anticholinesterase agents or other parasympathomimetic drugs, and cardiac arrest produced by stimulation of the vagus. Atropine may also lessen the degree of partial heart block when vagal activity is an etiologic factor. In some individuals with complete heart block, the idioventricular rate may be accelerated by atropine; in others, the rate is stabilized. In some patients with conduction defects, atropine may cause paradoxical atrioventricular (A-V) block and nodal rhythm.

Systemic doses of atropine slightly raise systolic and lower diastolic pressures and can produce significant postural hypotension. Such doses also slightly increase cardiac output and decrease central venous pressure. Atropine can dilate cutaneous blood vessels, particularly in the “blush” area (atropine flush), and may cause overheating due to suppression of sweat gland activity [see Warnings and Precautions (5.2)].

Pharmacokinetics

Atropine is well absorbed after intramuscular administration. Atropine is distributed throughout the various body tissues and fluids. Much of the drug is metabolized by enzymatic hydrolysis, particularly in the liver; from 13 to 50% is excreted unchanged in the urine. Atropine has been reported to be excreted in human milk [see Use in Specific Populations (8.2)]. Atropine readily crosses the placental barrier and enters the fetal circulation.

The approximate Cmax of atropine following 1.67 mg atropine given intramuscularly to adults by the 2 mg AtroPen® delivery system was 9.6 ± 1.5 (mean ± SEM) ng/mL. The mean Tmax was 3 minutes. The T½ of intravenous atropine in pediatric subjects over 2 years is 2.5 ± 1.2 (mean ± SD) hours; in adults 16–58 years the T½ is 3.0 ± 0.9 (mean ± SD) hours; in geriatric patients 65–75 years it is 10.0 ± 7.3 (mean ± SD) hours. The protein binding of atropine is 14 to 22% in plasma. There are gender differences in the pharmacokinetics of atropine. The AUC(0-inf) and Cmax were 15% higher in females than males. The half-life of atropine is slightly shorter (approximately 20 minutes) in females than males.

NONCLINICAL TOXICOLOGY

Carcinogenesis, Mutagenesis, Impairment of Fertility

Carcinogenesis

No adequate studies regarding the carcinogenic potential of atropine have been conducted.

Mutagenesis

Studies to assess the mutagenic potential of atropine have not been conducted.

Impairment of Fertility

In studies in which male rats were orally administered atropine (62.5 to 125 mg/kg) for one week prior to mating and throughout a 5-day mating period with untreated females, a dose-related decrease in fertility was observed. A no-effect dose for male reproductive toxicity was not established. The lowest dose tested was approximately 300 times (on a mg/m2 basis) the dose of atropine in a single autoinjector application.

Fertility studies of atropine in females have not been conducted.

How Supplied

The 2 mg Atropine autoinjector provides atropine base 1.67 mg/0.7 mL (equivalent to atropine sulfate 2 mg/0.7 mL) in a sterile solution for intramuscular injection.

The 2 mg Atropine autoinjector is supplied as 480 self-contained single-dose autoinjectors per box (NDC 71053-592-01).

Storage and Handling

Store at 20°C to 25°C (68°F to 77°F); excursions permitted between 15°C to 30°C (59°F to 86°F) [see USP Controlled Room Temperature].

Do Not Freeze.

PATIENT COUNSELING INFORMATION

Advise the patient to read the FDA-approved patient labeling (Instructions for Use).

Administration

Ensure that users understand the indications for and use of Atropine, including review of symptoms of poisoning and operation of the Atropine autoinjector [see Dosage and Administration (2.2)].

Seek Definitive Medical Care

If feasible and appropriate, advise patients that Atropine is an initial emergency treatment, that they need additional care at a healthcare facility.

Avoid Overheating

If feasible and appropriate, advise the patient to avoid a hot environment and excessive physical activity since atropine can inhibit sweating which can lead to overheating and heat injury.

Manufactured by:

RAFA LABORATORIES, LTD.

JERUSALEM,ISRAEL

Instructions for Use

ATROPINE

injection, for intramuscular use

2 mg Atropine single-dose autoinjector

If possible, a healthcare provider or someone who has been trained to identify and treat the symptoms of exposure to nerve agents or insecticides should give (administer) the Atropine autoinjector. If a healthcare provider is not available during an emergency,a patient or a caregiver might need to give the Atropine injection.

Individuals should not rely only on Atropine for protection from nerve agent or insecticide poisoning.

Patients and caregivers need to wear clothing to protect their skin and goggles and masks to protect their face and eyes when available to avoid exposure.

Leave the exposed (contaminated) area as quickly as possible.

Get medical help right away after exposure.

Step 1: Decide if the 2 mg Atropine autoinjector is right to use based on weight and age.

- The 2 mg Atropine autoinjector is for use only in adults and children weighing over 90 pounds (41 kg) (generally over 10 years of age).
- Do notuse the 2 mg Atropine autoinjector for children weighing 90 pounds (41 kg) and less (generally 10 years of age and younger). The dose of the 2 mg Atropine autoinjector cannot be changed.

Step 2: Decide if symptoms are mild or severe using Table 1 below.The number of injections needed depends on if there are 2 or more mild symptoms or if there are any severe symptoms.

Note: You may not see all of these symptoms in yourself or others exposed to a nerve agent or certain insecticide poisoning.

Table 1. Symptoms of Nerve Agent or Insecticide Poisoning
Mild symptoms include:; - Blurred vision - The black circle in the center of the colored part of the eye (pupil) is very small - Unexplained excessive teary eyes - Unexplained excessive runny nose - Increased saliva or drooling - Chest tightness, difficulty breathing, wheezing, or coughing - Shaking (tremors) throughout the body or muscle twitching - Nausea or vomiting - Stomach cramps or diarrhea - Fast heartbeat or pounding in your chest (tachycardia) - Slow heartbeat (bradycardia) | Severe symptoms include:; - Strange or confused behavior - Passing out (unconsciousness) - Severe breathing problems such as short, quick breaths through the mouth (gasping for air) - Large amount of fluid (secretions) coming from the mouth or nose - Severe muscle twitching, general weakness, or paralysis - Inability to control urine or stool (bowel movement) - Sudden uncontrollable or irregular movements of parts of your body (convulsions or seizures)

Step 3: Decide the number of Atropine autoinjectors to use based on if the symptoms are mild or severe. See Table 1and Figure 1.

Mild Symptoms (see Table 1)

First Dose: If you have or see someone with 2 or more mild symptomslisted in Table 1and exposure is known or suspected, give 1 injectionof Atropine into the outer thigh using the Atropine autoinjector. You can inject through clothing, but make sure pockets at the injection site are empty. Keep checking to see if symptoms continue or get worse. Get medical help right away.

Additional Doses: If at any time after the first dose(1 injection) the person who was exposed starts to have any of the severe symptoms listed in Table 1, you will need to give 2 more injectionsquickly one right after the other using a new Atropine autoinjector for each injection. Do notuse the same autoinjector more than one time. If you have given yourself the first injection, someone else should give you the second and third injections, if possible.

You can inject additional doses through clothing, but make sure pockets at the injection site are empty.

No more injections are needed if the person who was exposed does not get sever symptoms 10 to 15 minutes after the first dose (1 injection).

Severe Symptoms (see Table 1)

If you have or see someone with anyof the severe symptomslisted in Table 1and exposure is known or suspected, or you see an exposed person passed out (unconscious), give 3 injectionsinto the outer thigh quickly one right after the other, using 3 new autoinjectors.

You can inject through clothing, but make sure pockets at the injection site are empty. Get medical help right away.

Step 4: Instructions for how to use the Atropine autoinjector

A.) Hold the plastic sleeve on both sides of the dotted lines (perforation) and tear apart at the edge to open. Remove the autoinjector from the plastic sleeve.

Be careful not to place fingers on the green tip.

B.) Firmly hold the autoinjector with the green tip pointed down.

C.) Pull off the yellow safety cap with your other hand.

D.) Aim and firmly inject the green tip straight down (at a 90° angle) against the outer thigh. The autoinjector will give the medicine when you do this. You can inject through clothing, but make sure pockets at the injection site are empty.

Note: People who may not have a lot of fat at the injection siteshould also be injected in the outer thigh. Before giving the injection, pinch a fold of skin firmly on the outer thigh to provide a thicker area for the injection.

E.) Hold the autoinjector firmly in place for at least 10 secondsto allow the injection to finish.

F.) After 10 seconds, remove the autoinjector from the outer thigh and massage the injection site in a circle motion for several seconds.

Note: If you do not see the needle after removing it from the outer thigh, the injection is not completed.

Check to be sure the yellow safety cap has been removed.If the yellow safety cap has been removed, repeat Step 4 D) to Step 4 E) pressing more firmly against the outer thigh to activate the autoinjector.

If you still do not see the needle, use a new autoinjector and start over again at Step 4 A).

G.) After the injection, avoid contact with blood or the needle by carefully bending the needle back against the autoinjector using a hard surface. Use the bent needle as a hook to pin the used autoinjector to the clothing of the person who has been exposed. This will allow medical personnel to see the number of Atropine autoinjectors given. You can also put the used autoinjector back into the plastic sleeve and leave it next to the person or write the dose and number of autoinjectors used on a triage tag, hand, forehead, chest or other part of the body.

Move yourself and the exposed person away from the contaminated area right away. Get medical help right away.

Each autoinjector has only a single dose (1 injection) of medicine. If you need more than 1 injection,repeat the instructions in Step 4 using a new autoinjector for each injection.

This Instructions for Use has been approved by the U.S. Food and Drug Administration.

Manufactured by:

Rafa Laboratories, Ltd.

Jerusalem, Israel

Revised: 07/2019